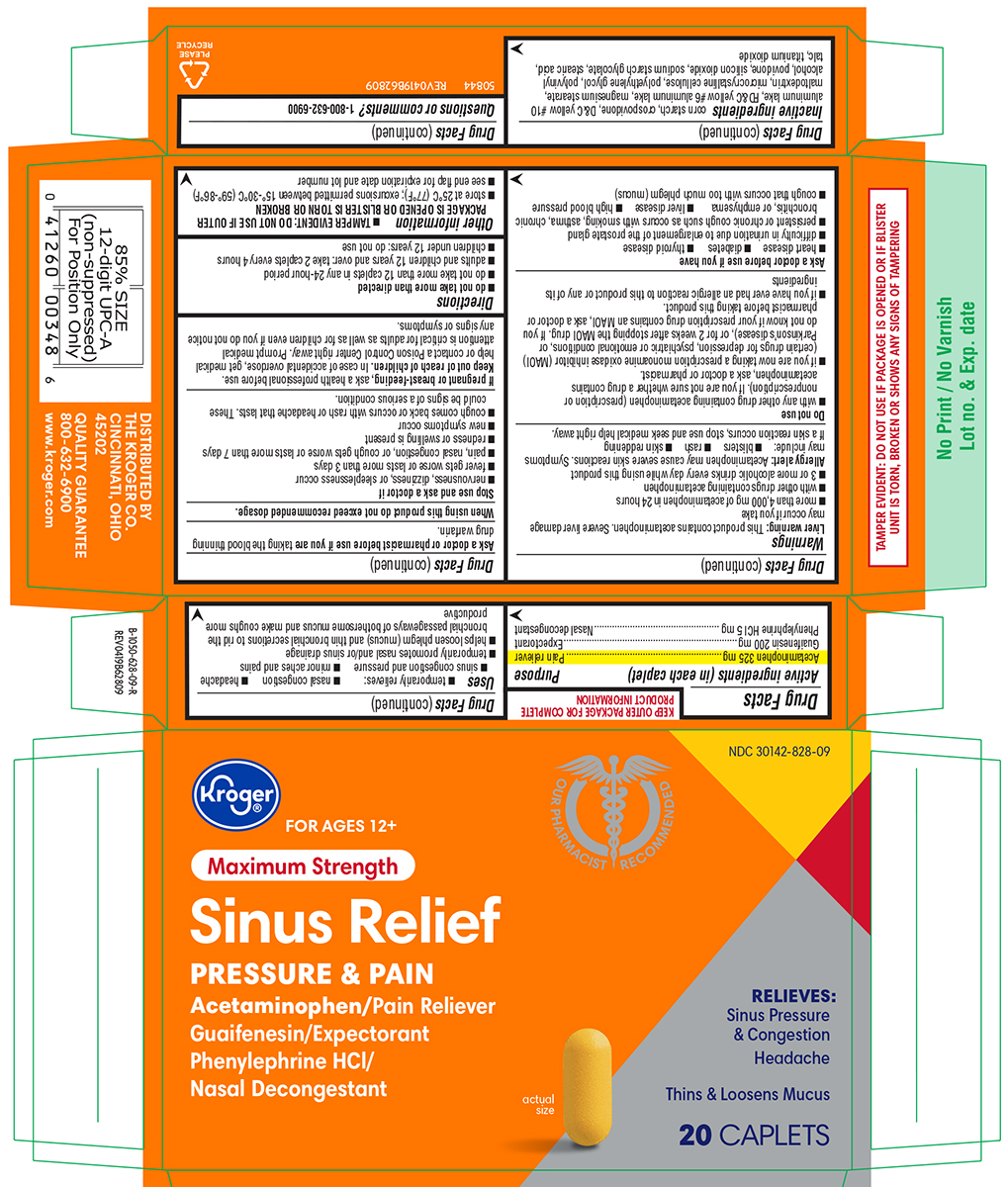 DRUG LABEL: Sinus Relief Pressure and Pain
NDC: 30142-828 | Form: TABLET, FILM COATED
Manufacturer: Kroger Company
Category: otc | Type: HUMAN OTC DRUG LABEL
Date: 20250827

ACTIVE INGREDIENTS: ACETAMINOPHEN 325 mg/1 1; GUAIFENESIN 200 mg/1 1; PHENYLEPHRINE HYDROCHLORIDE 5 mg/1 1
INACTIVE INGREDIENTS: STARCH, CORN; CROSPOVIDONE, UNSPECIFIED; D&C YELLOW NO. 10 ALUMINUM LAKE; FD&C YELLOW NO. 6 ALUMINUM LAKE; MAGNESIUM STEARATE; MALTODEXTRIN; MICROCRYSTALLINE CELLULOSE; POLYETHYLENE GLYCOL, UNSPECIFIED; POLYVINYL ALCOHOL, UNSPECIFIED; POVIDONE, UNSPECIFIED; SILICON DIOXIDE; SODIUM STARCH GLYCOLATE TYPE A POTATO; STEARIC ACID; TALC; TITANIUM DIOXIDE

Kroger 44-628 Delisted

Active ingredients (in each caplet)

Acetaminophen 325 mg
Guaifenesin 200 mg
Phenylephrine HCl 5 mg

Purpose

Pain reliever
Expectorant
Nasal decongestant

Uses

- temporarily relieves:
  - nasal congestion
  - headache
  - sinus congestion and pressure
  - minor aches and pains
- temporarily promotes nasal and/or sinus drainage
- helps loosen phlegm (mucus) and thin bronchial secretions to rid the bronchial passageways of bothersome mucus and make coughs more productive

Warnings

Liver warning: This product contains acetaminophen. Severe liver damage may occur if you take

- more than 4,000 mg of acetaminophen in 24 hours
- with other drugs containing acetaminophen
- 3 or more alcoholic drinks every day while using this product

Allergy alert: Acetaminophen may cause severe skin reactions. Symptoms may include:

- blisters
- rash
- skin reddening

If a skin reaction occurs, stop use and seek medical help right away.

Do not use

- with any other drug containing acetaminophen (prescription or nonprescription). If you are not sure whether a drug contains acetaminophen, ask a doctor or pharmacist.
- if you are now taking a prescription monoamine oxidase inhibitor (MAOI) (certain drugs for depression, psychiatric or emotional conditions, or Parkinson’s disease), or for 2 weeks after stopping the MAOI drug. If you do not know if your prescription drug contains an MAOI, ask a doctor or pharmacist before taking this product.
- if you have ever had an allergic reaction to this product or any of its ingredients

Ask a doctor before use if you have

- heart disease
- diabetes
- thyroid disease
- difficulty in urination due to enlargement of the prostate gland
- persistent or chronic cough such as occurs with smoking, asthma, chronic bronchitis, or emphysema
- liver disease
- high blood pressure
- cough that occurs with too much phlegm (mucus)

Ask a doctor or pharmacist before use if you are

taking the blood thinning drug warfarin.

When using this product

do not exceed recommended dosage.

Stop use and ask a doctor if

- nervousness, dizziness, or sleeplessness occur
- fever gets worse or lasts more than 3 days
- pain, nasal congestion, or cough gets worse or lasts more than 7 days
- redness or swelling is present
- new symptoms occur
- cough comes back or occurs with rash or headache that lasts. These could be signs of a serious condition.

If pregnant or breast-feeding,

ask a health professional before use.

Keep out of reach of children.

In case of accidental overdose, get medical help or contact a Poison Control Center right away. Prompt medical attention is critical for adults as well as for children even if you do not notice any signs or symptoms.

Directions

- do not take more than directed
- do not take more than 12 caplets in any 24-hour period
- adults and children 12 years and over: take 2 caplets every 4 hours
- children under 12 years: do not use

Other information

- TAMPER EVIDENT: DO NOT USE IF OUTER PACKAGE IS OPENED OR BLISTER IS TORN OR BROKEN
- store at 25°C (77°F); excursions permitted between 15°-30°C (59°-86°F)
- see end flap for expiration date and lot number

Inactive ingredients

corn starch, crospovidone, D&C yellow #10 aluminum lake, FD&C yellow #6 aluminum lake, magnesium stearate, maltodextrin, microcrystalline cellulose, polyethylene glycol, polyvinyl alcohol, povidone, silicon dioxide, sodium starch glycolate, stearic acid, talc, titanium dioxide

Questions or comments?

1-800-632-6900

Principal display panel

Kroger®

NDC 30142-828-09

FOR AGES 12+

Maximum Strength

Sinus Relief
PRESSURE & PAIN

Acetaminophen / Pain Reliever
Guaifenesin / Expectorant
Phenylephrine HCl /
Nasal Decongestant

RELIEVES:
Sinus Pressure
& Congestion
Headache

Thins & Loosens Mucus

20
CAPLETS

actual
size

Our Pharmacist Recommended

TAMPER EVIDENT: DO NOT USE IF PACKAGE IS OPENED OR IF BLISTER
UNIT IS TORN, BROKEN OR SHOWS ANY SIGNS OF TAMPERING

DISTRIBUTED BY
THE KROGER CO.
CINCINNATI, OHIO
45202

QUALITY GUARANTEE
800-632-6900
www.kroger.com

50844 REV0419B62809

Kroger 44-628